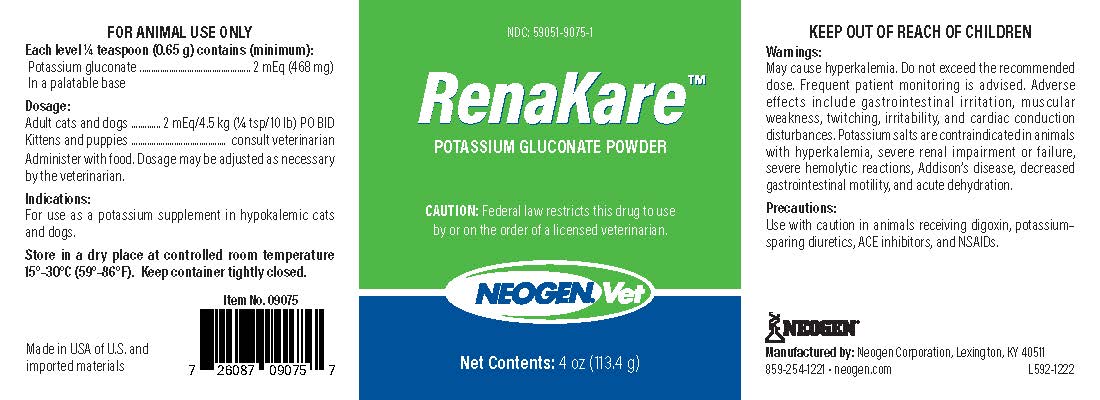 DRUG LABEL: RenaKare
NDC: 59051-9075 | Form: POWDER
Manufacturer: Neogen Corporation-Mercer Rd
Category: animal | Type: PRESCRIPTION ANIMAL DRUG LABEL
Date: 20230221

ACTIVE INGREDIENTS: POTASSIUM GLUCONATE 468 mg/0.65 g
INACTIVE INGREDIENTS: PORK LIVER

DESCRIPTION

RenaKare™

Potassium Gluconate Powder

CAUTION: Federal law restricts this drug to use by or on the order of a licensed veterinarian.

Each level ¼ teaspoon (0.65 g) contains (minimum):

Potassium gluconate......................2 mEq (468 mg)

in a palatable base

Dosage:

Adult cats and dogs..............2 mEq/4.5 kg (¼ tsp/10 lb) PO BID

Kittens and puppies..............Consult veterinarian

Administer with food. Dosage may be adjusted as necessary by the veterinarian.

Item No. 09075

Indications:

For use as a potassium supplement in hypokalemic cats and dogs.

Warnings:

May cause hyperkalemia. Do not exceed the recommended dose. Frequent patient monitoring is advised. Adverse effects include gastrointestinal irritation, muscular weakness, twitching, irritability, and cardiac conduction distrubances. Potassium salts are contraindicated in animals with hyperkalemia, severe renal impairment or failure, sever hemolytic reactions, Addison's disease, decreased gastrointestinal motility, and acute dehydration.

Precaustions:

Use with caution in animals receiving digoxin, potassium-sparing diuretics, ACE inhibitors, and NSAIDS.

Lot No.:

Exp. Date:

Manufactured by Neogen Corporation

Lexington, KY 40511 USA • 859/254-1221

L592-91908

PRINCIPAL DISPLAY PANEL - 4 oz Bottle

NDC: 59051-9075-1

RenaKare™

Potassium Gluconate Powder

CAUTION: Federal law restricts this drug to use by or on the order of a licensed veterinarian.

NEOGEN.Vet

Net Contents: 4 oz